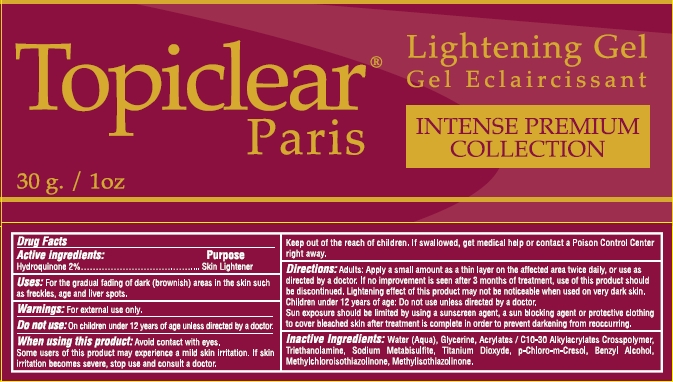 DRUG LABEL: Topiclear Paris
NDC: 66129-840 | Form: GEL
Manufacturer: International Beauty Exchange
Category: otc | Type: HUMAN OTC DRUG LABEL
Date: 20120516

ACTIVE INGREDIENTS: HYDROQUINONE .6 g/30 g
INACTIVE INGREDIENTS: WATER; ALCOHOL; GLYCERIN; CARBOMER COPOLYMER TYPE A; TROLAMINE; SODIUM METABISULFITE; EDETATE DISODIUM

Drug Facts

ACTIVE INGREDIENT

Hydroquinone 2%

WARNINGS

For external use only

DO NOT USE

On children under 12 years of age unless directed by a doctor

WHEN USING

Avoid contact with eyes.

PURPOSE

Skin Lightener

INDICATIONS AND USAGE

For the gradual fading of dark (brownish) areas in the skin such as freckles, age and liver spots

DOSAGE AND ADMINISTRATION

Apply a small amount as a thin layer on the affected area twice daily, or use as directed by a doctor

KEEP OUT OF REACH OF CHILDREN

If swallowed, get medical help or contact a Poison Control Center right away

INACTIVE INGREDIENT

WATER, CETOSTEARYL ALCOHOL, GLYCERIN, TROLAMINE, CARBOMER COPOLYMER TYPE A, SODIUM METABISULFITE, EDETATE DISODIUM